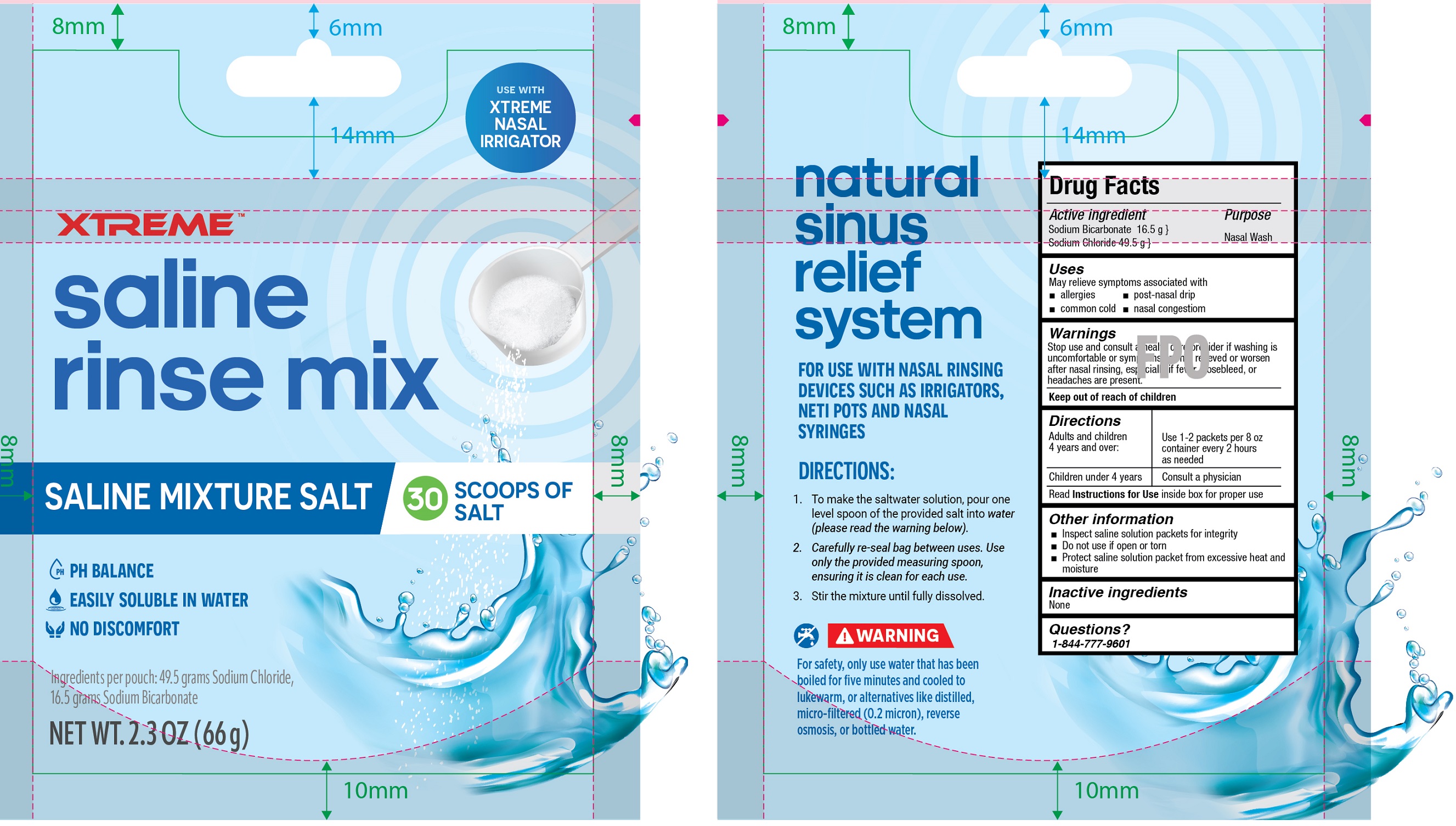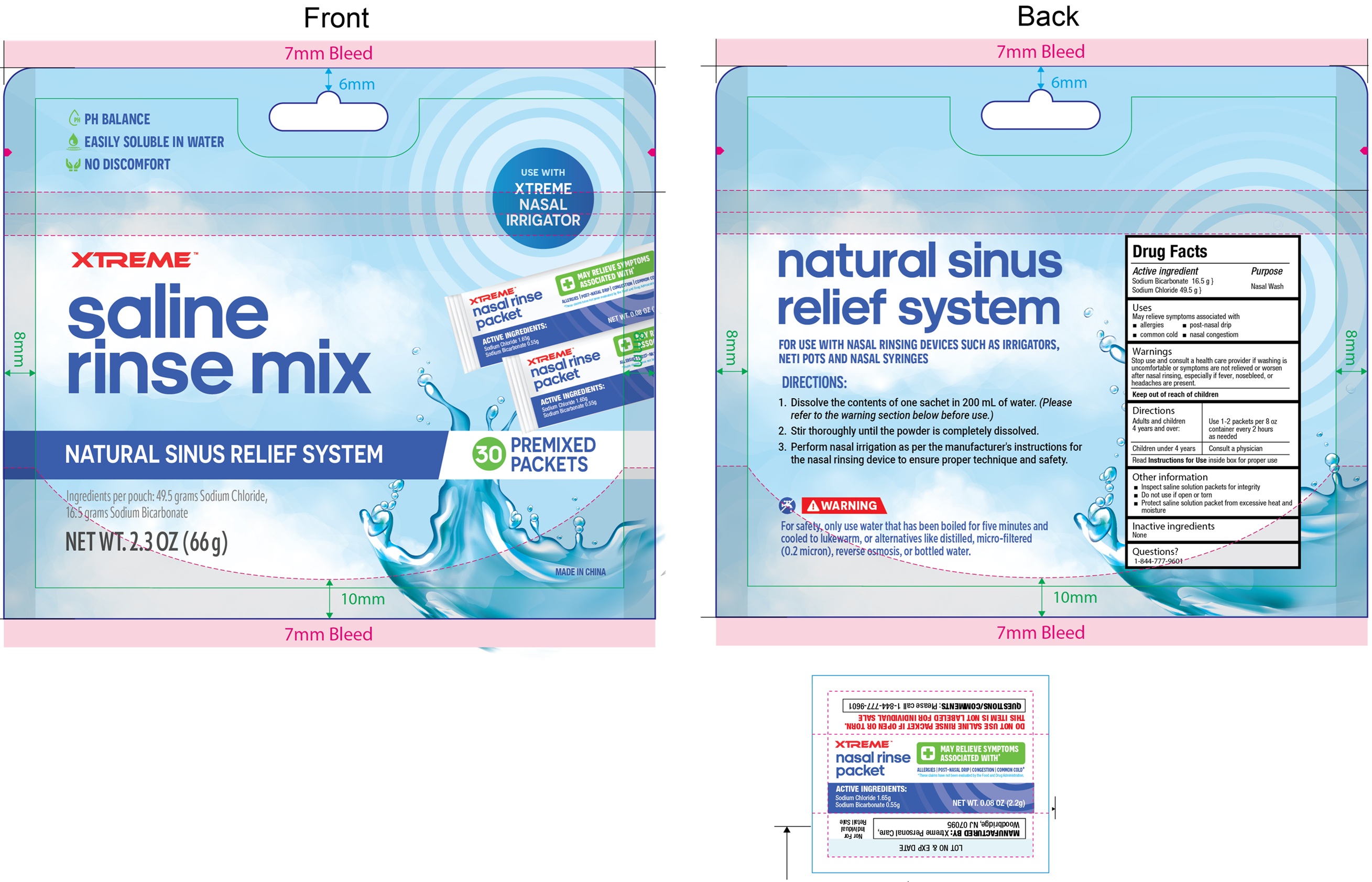 DRUG LABEL: Xtreme Saline Rinse Mix
NDC: 74851-010 | Form: POWDER, FOR SOLUTION
Manufacturer: Xtreme Personal Care Inc
Category: otc | Type: HUMAN OTC DRUG LABEL
Date: 20250617

ACTIVE INGREDIENTS: SODIUM BICARBONATE 16.5 g/66 g; SODIUM CHLORIDE 49.5 g/66 g

Xtreme Saline Rinse Mix

Active ingredient

Sodium Bicarbonate 16.5 g
Sodium Chloride 49.5 g

Purpose

Nasal Wash

Uses

May relieve symptoms associated with
• allergies • post-nasal drip
• common cold • Nasal congestiom

Warnings

Stop use and consult a health

care provider if washing is uncomfortable or symptoms not relieved or worsen after nasal rinsing, especially if fever, nosebleed, or headaches are present.

Directions

- Use 1 packet per 200 ML as needed

Adults and children 4 years and over: | Use 1-2 packets per 8 oz container every 2 hours as needed
Children under 4 years | Consult a physician

Read Instructions for Use inside box for proper use

Other information

- Inspect saline solution packets for integrity
- Do not use if open or torn
- Protect saline solution packet from excessive heat and moisture

Inactive ingredients

None

Questions?

1-844-777-9601